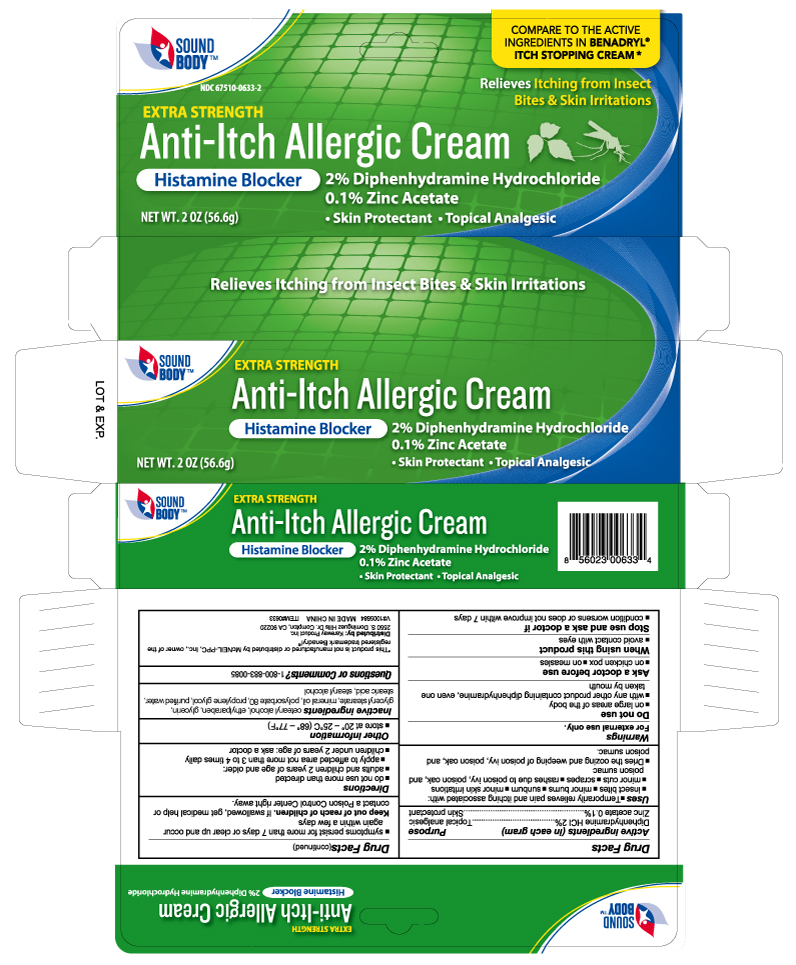 DRUG LABEL: Anti-Itch
NDC: 67510-0633 | Form: CREAM
Manufacturer: Kareway Product, Inc.
Category: otc | Type: HUMAN OTC DRUG LABEL
Date: 20230217

ACTIVE INGREDIENTS: DIPHENHYDRAMINE HYDROCHLORIDE 2 g/100 g; ZINC ACETATE 0.1 g/100 g
INACTIVE INGREDIENTS: STEARYL ALCOHOL; CETYL ALCOHOL; GLYCERIN; GLYCERYL 1-STEARATE; MINERAL OIL; ETHYLPARABEN; POLYSORBATE 60; STEARIC ACID; PROPYLENE GLYCOL; WATER

Soundbody Anti-itch Cream

Active ingredients (in each gram)

Diphenhydramine HCl 2%

Zinc acetate 0.1%

Purpose

Topical analgesic

Skin protectant

Uses

- temporarily relieves pain and itching associated with:
- insect bites
- minor burns
- sunburn
- minor skin irritations
- minor cuts
- scrapes
- rashes due to poison ivy, poison oak or poison sumac
- dries the oozing and weeping of poison ivy, poison oak, and poison sumac

Warnings

For external use only.

Do not use

- on large areas of the body
- with any other product containing diphenhydramine, even one taken by mouth

When using this product

- avoid contact with eyes

Stop use and ask a doctor if

- condition worsens or does not improve within 7 days
- symptoms persist for more than 7 days or clear up and occur again within a few days

Keep out of reach of children

If swallowed, get medical help or contact a Poison Control Center right away.

Directions

- do not use more often than directed
- adults and children 2 years of age and older:
- apply to affected area not more than 3 to 4 times daily
- children under 2 years of age: ask a doctor

Other information

- store at 20° - 25°C (68° - 77°F)

Inactive ingredients

cetearyl alcohol, ethylparaben, glycerin, glyceryl stearate, mineral oil, polysorbate 80, propylene glycol, stearic acid, stearyl alcohol, water

Questions or Comments?

1-800-883-0085

Package label

Anti-Itch Cream